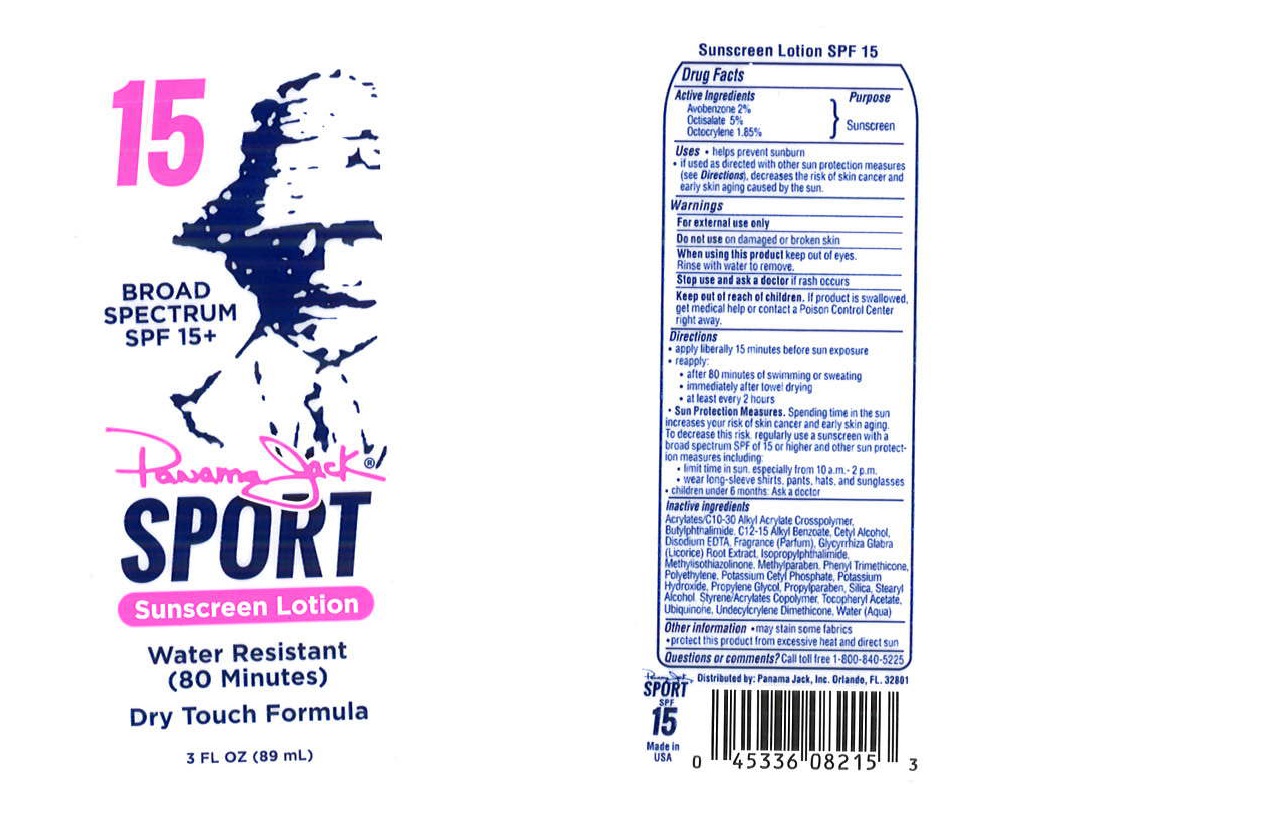 DRUG LABEL: Panama Jack
NDC: 58443-0159 | Form: LOTION
Manufacturer: Prime Enterprises Inc.
Category: otc | Type: HUMAN OTC DRUG LABEL
Date: 20200117

ACTIVE INGREDIENTS: AVOBENZONE 19.6 mg/1 mL; OCTISALATE 49 mg/1 mL; OCTOCRYLENE 18.13 mg/1 mL
INACTIVE INGREDIENTS: METHYLPARABEN; CETYL ALCOHOL; EDETATE DISODIUM; PHENYL TRIMETHICONE; PROPYLPARABEN; METHYLISOTHIAZOLINONE; ISOPROPYLPHTHALIMIDE; POTASSIUM CETYL PHOSPHATE; HIGH DENSITY POLYETHYLENE; LICORICE; PROPYLENE GLYCOL; POTASSIUM HYDROXIDE; ALKYL (C12-15) BENZOATE; N-BUTYLPHTHALIMIDE; UBIQUINONE Q2; SILICON DIOXIDE; (C10-C30)ALKYL METHACRYLATE ESTER; ALPHA-TOCOPHEROL ACETATE; WATER; STEARYL ALCOHOL; STYRENE/ACRYLAMIDE COPOLYMER (MW 500000)

Panama Jack Broad Spectrum SPF 15 Sport

Active Ingredients

Avobenzone 2%

Octisalate 5%

Octocrylene 1.85%

Purpose

Sunscreen

Uses

- helps prevent sunburn.
- if used as directed with other sun protection measures (see Directions), decreases the risk of skin cancer and early skin aging caused by the sun.

WARNINGS

For external use only.

Do not use on damaged or broken skin

When using this product keep out of eyes. Rinse with water to remove.

Stop use and ask a doctor if rash occurs.

Keep out of reach of children. If product is swallowed, get medical help or contact a Poison Control Center right away.

Directions

- apply liberally 15 minutes before sun exposure.
- reapply:
- after 80 minutes of swimming or sweating.
- immediately after towel drying.
- at least every 2 hours.
- Sun Protection Measures. Spending time in the sun increases your risk of skin cancer and early skin aging. To decrease this risk, regularly use a sunscreen with a broad spectrum SPF of 15 or higher and other sun protection measures including:
- limit time in the sun, especially from 10 a.m. – 2 p.m.
- wear long-sleeve shirts, pants, hats, and sunglasses.
- children under 6 months: Ask a doctor.

Inactive Ingredients

Acrylates/C10-30 Alkyl Acrylate Crosspolymer, Butylphthalimide, C12-15 Alkyl Benzoate, Cetyl Alcohol, Disodium EDTA, Fragrance (Parfum), Glycyrrhiza Glabra (Licorice) Root Extract, Isopropylphthalimide, Methylisothiazolinone, Methylparaben, Phenyl Trimethicone, Polyethylene, Potassium Cetyl Phosphate, Potassium Hydroxide, Propylene Glycol, Propylparaben, Silica, Stearyl Alcohol, Styrene/Acrylates Copolymer, Tocopheryl Acetate, Ubiquinone, Undecylcrylene Dimethicone, Water (Aqua)

Other Information

- may stain some fabrics
- protect this product from excesive heat and direct sun.

Questions or comments?

Call toll free 1-800-840-5225